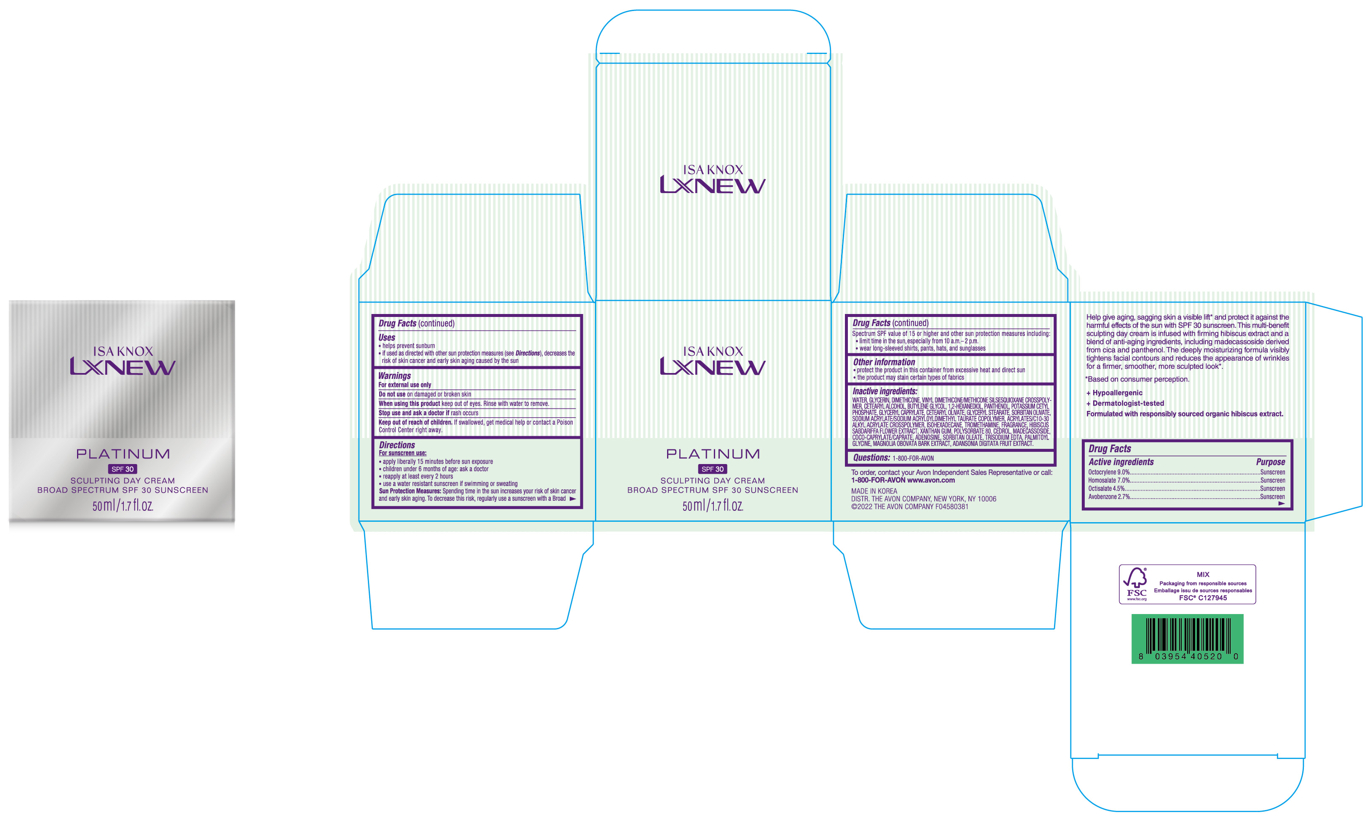 DRUG LABEL: ISA KNOX LXNEW PLATINUM SCULPTING DAY BROAD SPECTRUM SPF 30 SUNSCREEN
NDC: 53208-210 | Form: CREAM
Manufacturer: LG H&H Co., Ltd.
Category: otc | Type: HUMAN OTC DRUG LABEL
Date: 20250101

ACTIVE INGREDIENTS: OCTISALATE 4.5 g/50 mL; HOMOSALATE 7 g/50 mL; AVOBENZONE 2.7 g/50 mL; OCTOCRYLENE 9 g/50 mL
INACTIVE INGREDIENTS: WATER

53208-210-01 Isa Knox Lxnew Platinum Sculpting Day Cream Broad Spectrum SPF 30 Sunscreen

ACTIVE INGREDIENTS

Avobenzone 2.7%
Homosalate 7%
Octisalate 4.5%
Octocrylene 9%

PURPOSE

SUNSCREEN

USES

- Helps prevent sunburn
- If used as directed with other sun protection measures (see Directions), decreases the risk of skin cancer and early skin aging caused by the sun

WARNINGS

For external use only

- Do not useon damaged or broken skin.

WHEN USING

- When using this productkeep out of eyes. Rinse with water to remove.

- Stop use and ask a doctor ifrash occurs.

- Keep out of reach of children.If swallowed, get medical help or contact a Poison Control Center right away.

DIRECTIONS

For sunscreen use:

- apply liberally 15 minutes before sun exposure
- children under 6 months of age: ask a doctor
- reapply at least every 2 hours
- use a water resistant sunscreen if swimming or sweating
- Sun Protection Measures.Spending time in the sun increases your risk of skin cancer and early skin aging. To decrease this risk, regularly use a sunscreen with a Broad Spectrum SPF value of 15 or higher and other sun protection measures including:
- limit time in the sun, especially from 10 a.m.-2 p.m.
- wear long-sleeved shirts, pants, hats, and sunglasses

INACTIVE INGREDIENTS

WATER, GLYCERIN,

OTHER INFORMATION

- protect the product in this container from excessive heat and direct sun
- the product may stain certain types of fabrics

QUESTIONS?

1-800-FOR-AVON

+ Hypoallergenic

+ Dermatologist-tested

Formulated with responsibly sourced organic hibiscus extract.

To order, contact your Avon Indenpendent Sales Representative or call:
1-800-FOR-AVONwww.avon.com

MADE IN KOREA
DISTR. THE AVON COMPANY, NEW YORK, NY 10006
©2022 THE AVON COMPANY

PRINCIPAL DISPLAY PANEL

ISA KNOX

LXNEW

PLATINUM

SPF 30

SCULPTING DAY CREAM
BROAD SPECTRUM SPF 30 SUNSCREEN

50 ml/1.7 fl.oz.